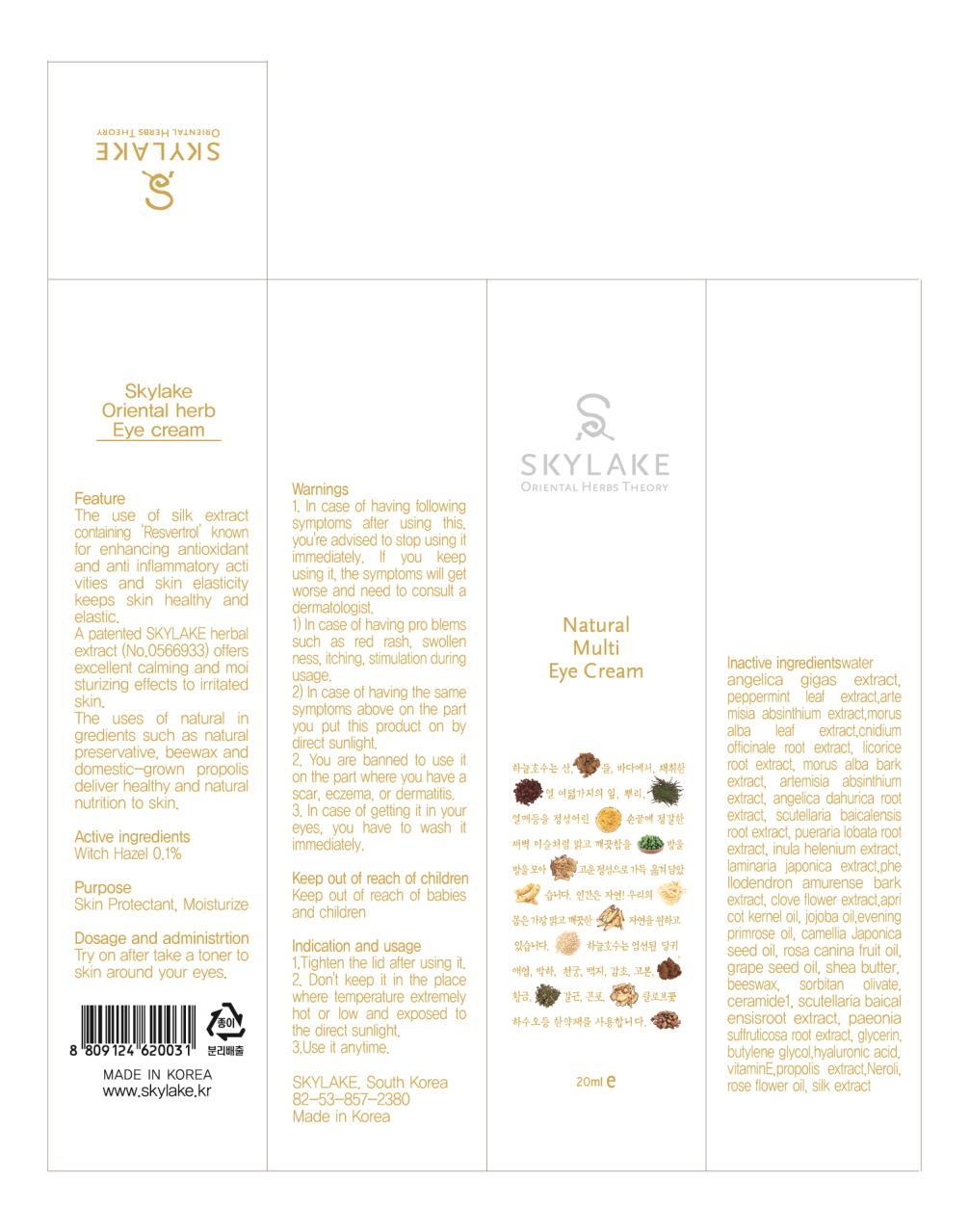 DRUG LABEL: SKYLAKE ORIENTAL HERB EYE
NDC: 53798-010 | Form: CREAM
Manufacturer: SKYLAKE
Category: otc | Type: HUMAN OTC DRUG LABEL
Date: 20121220

ACTIVE INGREDIENTS: Witch Hazel 0.02 g/20 mL
INACTIVE INGREDIENTS: water; glycerin; butylene glycol

ACTIVE INGREDIENT

Active ingredients: Witch Hazel 0.1%

INACTIVE INGREDIENT

Inactive ingredient lists:
water, angelica gigas extract, peppermint leaf extract, artemisia absinthium extract, Morus Alba Leaf Extract, cnidium officinale root extract, glycyrrhiza glabra (licorice) root extract, morus alba bark extract, artemisia absinthium extract, angelica dahurica root extract, scutellaria baicalensis root extract, pueraria lobata root extract, inula helenium extract, laminaria japonica extract, phellodendron amurense bark extract, clove flower extract, apricot kernel oil, jojoba oil, evening primrose oil, Camellia Japonica Seed Oil, rosa canina fruit oil, grape seed oil, shea butter, beeswax, sorbitan olivate, Ceramide1, scutellaria baicalensis root extract, Paeonia Suffruticosa Root Extract, glycerin, butylene glycol, hyaluronic acid, vitaminE, Propolis Extract, Bitter Orange Flower Extract(Neroli), Rose Flower Oil, Silk extract

PURPOSE

Purpose: Skin Protectant, Moisturize

WARNINGS

1. In case of having following symptoms after using this. you're advised to stop using it immediately. If you keep using it, the symptoms will get worse and need to consult a dermatologist.
1) In case of having problems such as red rash, swollenness, itching, stimulation during usage.
2) In case of having the same symptoms above on the part you put this product on by direct sunlight.
2. You are banned to use it on the part where you have a scar, eczema, or dermatitis.
3. In case of getting it in your eyes, you have to wash it immediately.

KEEP OUT OF REACH OF CHILDREN

Keep out of reach of babies and children

INDICATIONS AND USAGE

Indication and usage:
1. Tighten the lid after using it.
2. Don't keep it in the place where temperature extremely hot or low and exposed to the direct sunlight.
3. Use it anytime.

DOSAGE AND ADMINISTRATION

- The use of silk extract containing ‘Resveratrol’ known for enhancing antioxidant and anti-inflammatory activities and skin elasticity keeps skin healthy and elastic.
- A patented SKYLAKE herbal extract (No. 0566933) offers excellent calming and moisturizing effects to irritated skin.
- The uses of natural ingredients such as natural preservative, bee wax and domestic-grown propolis deliver healthy and natural nutrition to skin.